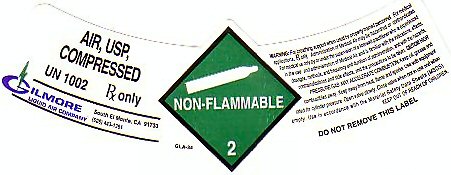 DRUG LABEL: AIR
NDC: 51012-003 | Form: GAS
Manufacturer: Gilmore Liquid Air Co.
Category: prescription | Type: HUMAN PRESCRIPTION DRUG LABEL
Date: 20241021

ACTIVE INGREDIENTS: AIR 20.5 L/100 L

Air

AIR, USP COMPRESSED LABEL

AIR, USP, COMPRESSED UN 1002 NON-FLAMMABLE-2 Rx ONLY

WARNING: FOR BREATHING SUPPORT WHEN USED BY PROPERLY TRAINED PERSONNEL. FOR MEDICAL APPLICATIONS Rx ONLY. ADMINISTRATION OF MEDICAL AIR MAY BE HAZARDOUS OR CONTRAINDICATED. FOR MEDICAL USE ONLY BY OR UNDER THE SUPERVISION OF A LICENSED PRACTITIONER WHO IS EXPERIENCED IN THE USE AND ADMINISTRATION OF MEDICAL AIR AND IS FAMILIAR WITH THE INDICATIONS, EFFECTS, DOSAGES, METHODS, AND FREQUENCY AND DURATION OF ADMINISTRATION, AND WITH THE HAZARDS AND PRECAUTIONS TO BE TAKEN. CAUTION: HIGH PRESSURE GAS MAY ACCELERATE COMBUSTION. KEEP OIL GREASE AND COMBUSTIBLES AWAY. KEEP AWAY FROM HEAT, FLAME AND SPARKS. USE WITH EQUIPMENT RATED FOR CYLINDER PRESSURE. OPEN VALVE SLOWLY. CLOSE VALVE WHEN NOT IN USE AND WHEN EMPTY. USE IN ACCORDANCE WITH THE MATERIAL SAFETY DATA SHEET (MSDS) KEEP OUT OF REACH OF CHILDREN. DO NOT REMOVE THIS PRODUCT LABEL.